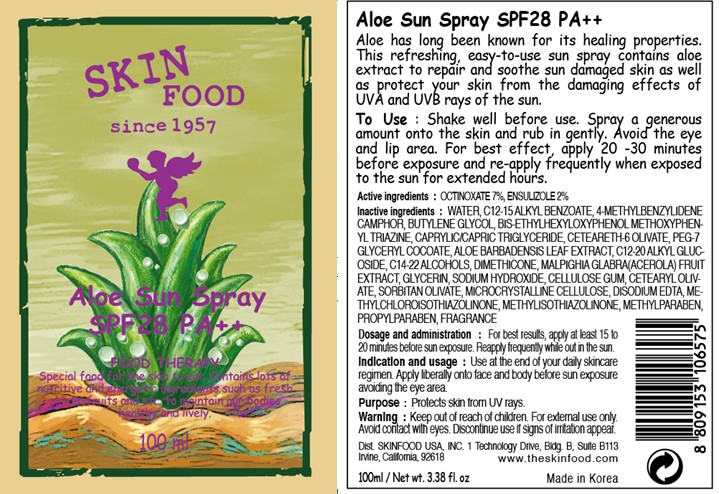 DRUG LABEL: ALOE SUN
NDC: 76214-019 | Form: SPRAY
Manufacturer: SKINFOOD CO., LTD.
Category: otc | Type: HUMAN OTC DRUG LABEL
Date: 20110908

ACTIVE INGREDIENTS: OCTINOXATE 7 mL/100 mL; ENSULIZOLE 2 mL/100 mL
INACTIVE INGREDIENTS: WATER; ENZACAMENE; ALKYL (C12-15) BENZOATE; BUTYLENE GLYCOL; BEMOTRIZINOL; MEDIUM-CHAIN TRIGLYCERIDES; ALOE VERA LEAF; C12-20 ALKYL GLUCOSIDE; C14-22 ALCOHOLS; DIMETHICONE; GLYCERIN; METHYLPARABEN; SODIUM HYDROXIDE; CARBOXYMETHYLCELLULOSE SODIUM; CETEARYL OLIVATE; SORBITAN OLIVATE; PROPYLPARABEN; EDETATE DISODIUM; METHYLCHLOROISOTHIAZOLINONE; METHYLISOTHIAZOLINONE

Drug Facts

Active ingredients: OCTINOXATE 7%, ENSULIZOLE 2%

Inactive ingredients:
WATER, C12-15 ALKYL BENZOATE, 4-METHYLBENZYLIDENE CAMPHOR, BUTYLENE GLYCOL, BIS-ETHYLHEXYLOXYPHENOL METHOXYPHENYL TRIAZINE, CAPRYLIC/CAPRIC TRIGLYCERIDE, CETEARETH-6 OLIVATE, PEG-7 GLYCERYL COCOATE, ALOE BARBADENSIS LEAF EXTRACT, C12-20 ALKYL GLUCOSIDE, C14-22 ALCOHOLS, DIMETHICONE, MALPIGHIA GLABRA(ACEROLA) FRUIT EXTRACT, GLYCERIN, SODIUM HYDROXIDE, CELLULOSE GUM, CETEARYL OLIVATE, SORBITAN OLIVATE, MICROCRYSTALLINE CELLULOSE, DISODIUM EDTA, ETHYLCHLOROISOTHIAZOLINONE, METHYLISOTHIAZOLINONE, METHYLPARABEN, PROPYLPARABEN, FRAGRANCE

Purpose: Protects skin from UV rays.

Warnings:
For external use only. Avoid contact with eyes.
Discontinue use if signs of irritation appear.

Keep out of reach of children:
Keep out of reach of children.

Indication and usage:
Use at the end of your daily skincare regimen. Apply liberally onto face and body before sun exposure avoiding the eye area.

Dosage and administration:
For best results, apply at least 15 to 20 minutes before sun exposure.
Reapply frequently while out in the sun.